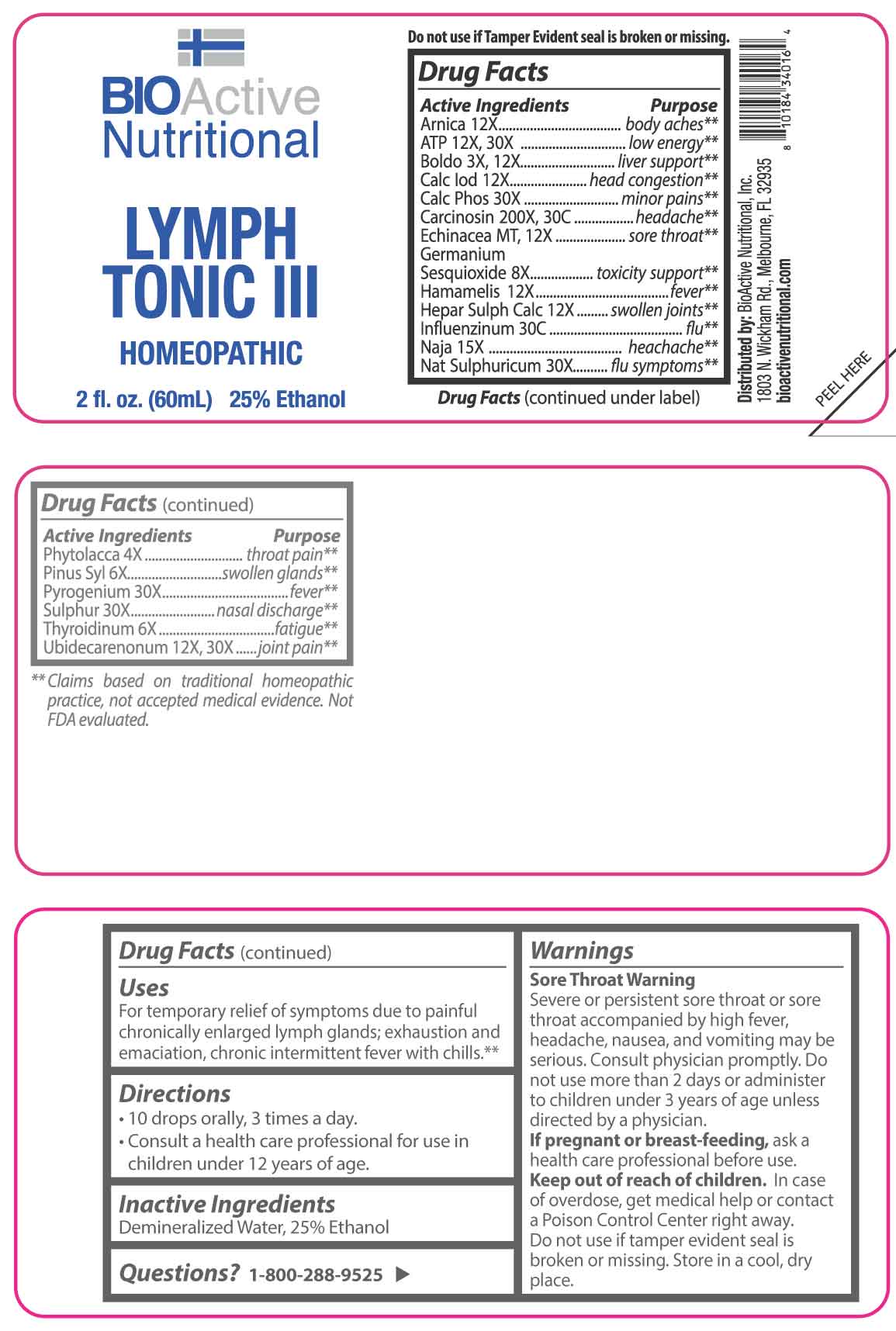 DRUG LABEL: Lymph Tonic III
NDC: 43857-0659 | Form: LIQUID
Manufacturer: BioActive Nutritional, Inc.
Category: homeopathic | Type: HUMAN OTC DRUG LABEL
Date: 20251229

ACTIVE INGREDIENTS: ECHINACEA ANGUSTIFOLIA WHOLE 1 [hp_X]/1 mL; PEUMUS BOLDUS LEAF 3 [hp_X]/1 mL; PHYTOLACCA AMERICANA ROOT 4 [hp_X]/1 mL; PINUS SYLVESTRIS LEAFY TWIG 6 [hp_X]/1 mL; THYROID 6 [hp_X]/1 mL; GERMANIUM SESQUIOXIDE 8 [hp_X]/1 mL; ARNICA MONTANA WHOLE 12 [hp_X]/1 mL; CALCIUM IODIDE 12 [hp_X]/1 mL; HAMAMELIS VIRGINIANA ROOT BARK/STEM BARK 12 [hp_X]/1 mL; CALCIUM SULFIDE 12 [hp_X]/1 mL; ADENOSINE TRIPHOSPHATE DISODIUM 12 [hp_X]/1 mL; UBIDECARENONE 12 [hp_X]/1 mL; NAJA NAJA VENOM 15 [hp_X]/1 mL; TRIBASIC CALCIUM PHOSPHATE 30 [hp_X]/1 mL; SODIUM SULFATE 30 [hp_X]/1 mL; RANCID BEEF 30 [hp_X]/1 mL; SULFUR 30 [hp_X]/1 mL; HUMAN BREAST TUMOR CELL 200 [hp_X]/1 mL; INFLUENZA A VIRUS WHOLE 30 [hp_C]/1 mL; INFLUENZA A VIRUS A/DARWIN/6/2021 (H3N2) WHOLE 30 [hp_C]/1 mL; INFLUENZA B VIRUS B/AUSTRIA/1359417/2021 BVR-26 WHOLE 30 [hp_C]/1 mL; INFLUENZA B VIRUS B/PHUKET/3073/2013 BVR-1B WHOLE 30 [hp_C]/1 mL
INACTIVE INGREDIENTS: WATER; ALCOHOL

DRUG FACTS:

ACTIVE INGREDIENT:

Arnica Montana 12X, Adenosinum Triphosphoricum Dinatrum 12X, 30X, Boldo 3X, 12X, Calcarea Iodata 12X, Calcarea Phosphorica 30X, Carcinosin 200X, 30C, Echinacea MT, 12X, Germanium Sesquioxide 8X, Hamamelis Virginiana 12X, Hepar Sulphuris Calcareum 12X, Influenzinum 30C, Naja Tripudians 15X, Natrum Sulphuricum 30X, Phytolacca Decandra 4X, Pinus Sylvestris 6X, Pyrogenium 30X, Sulphur 30X, Thyroidinum 6X, Ubidecarenonum 12X, 30X.

PURPOSE:

Arnica Montana – body aches,** Adenosinum Triphosphoricum Dinatrum – low energy,** Boldo – liver support,** Calcarea Iodata – head congestion,** Calcarea Phosphorica – minor pains,** Carcinosin - headache,** Echinacea – sore throat,** Germanium Sesquioxide – toxicity support,** Hamamelis Virginiana - fever,** Hepar Sulphuris Calcareum – swollen joints,** Influenzinum - flu,** Naja Tripudians - headache,** Natrum Sulphuricum – flu symptoms,** Phytolacca Decandra – throat pain,** Pinus Sylvestris – swollen glands,** Pyrogenium - fever,** Sulphur – nasal discharge,** Thyroidinum - fatigue,** Ubidecarenonum – joint pain**

**Claims based on traditional homeopathic practice, not accepted medical evidence. Not FDA evaluated.

USES:

For temporary relief of symptoms due to painful chronically enlarged lymph glands; exhaustion and emaciation, chronic intermittent fever with chills.**

**Claims based on traditional homeopathic practice, not accepted medical evidence. Not FDA evaluated.

WARNINGS:

Sore Throat Warning

Severe or persistent sore throat or sore throat accompanied by high fever, headache, nausea, and vomiting may be serious. Consult physician promptly. Do not use more than 2 days or administer to children under 3 years of age unless directed by a physician.

If pregnant or breast-feeding, ask a health care professional before use.

Keep out of reach of children. In case of overdose, get medical help or contact a Poison Control Center right away.

Do not use if tamper evident seal is broken or missing.

Store in a cool, dry place.

KEEP OUT OF REACH OF CHILDREN:

In case of overdose, get medical help or contact a Poison Control Center right away.

DIRECTIONS:

• 10 drops orally, 3 times a day.

• Consult a health care professional for use in children under 12 years of age.

INACTIVE INGREDIENTS:

Demineralized Water, 25% Ethanol

QUESTIONS:

Distributed by:
BioActive Nutritional, Inc.
1803 N. Wickham Rd.
Melbourne, FL 32935
bioactivenutritional.com

1-800-288-9525

PACKAGE LABEL DISPLAY:

BIOActive Nutritional

LYMPH TONIC III

HOMEOPATHIC

2 fl. oz. (60 mL)